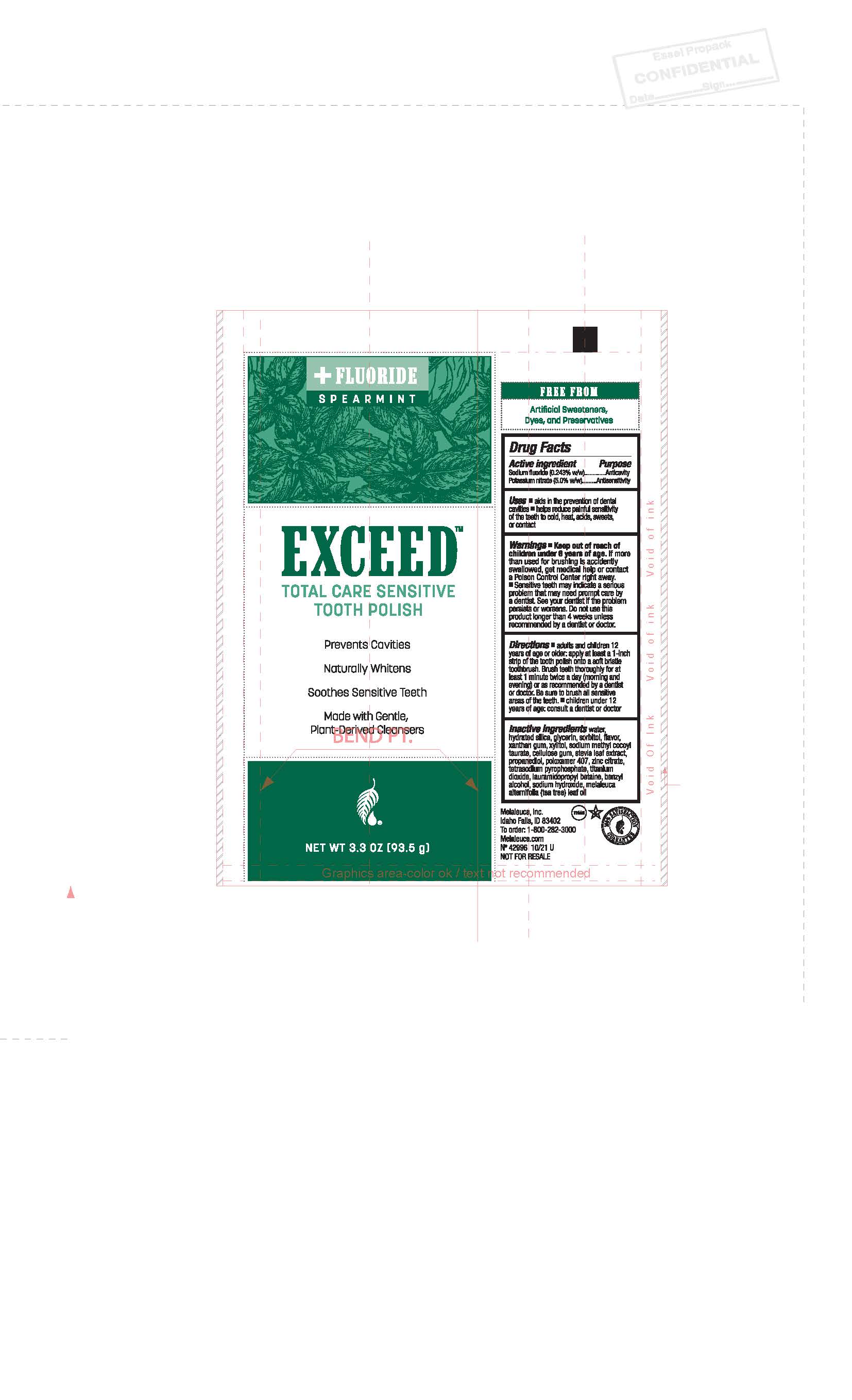 DRUG LABEL: Exceed Total Care Sensitive
NDC: 54473-337 | Form: PASTE, DENTIFRICE
Manufacturer: Melaleuca, Inc
Category: otc | Type: HUMAN OTC DRUG LABEL
Date: 20251231

ACTIVE INGREDIENTS: POTASSIUM NITRATE 0.2272 g/93.5 g; SODIUM FLUORIDE 4.675 g/93.5 g
INACTIVE INGREDIENTS: HYDRATED SILICA; POLOXAMER 407; PROPANEDIOL; MELALEUCA ALTERNIFOLIA LEAF; WATER; XANTHAN GUM; XYLITOL; CARBOXYMETHYLCELLULOSE; ZINC CITRATE; SODIUM METHYL COCOYL TAURATE; REBAUDIOSIDE A; SORBITOL; BENZYL ALCOHOL; SODIUM PYROPHOSPHATE; GLYCERIN; TITANIUM DIOXIDE; LAURAMIDOPROPYL BETAINE; SODIUM HYDROXIDE

Exceed Total Care Sensitive Tooth Polish - Spearmint

Uses

- aids in the prevention of dental cavaties
- helps reducee painful sensitivity of the teeth to cold, heat, acids, sweets or contact

Warnings

- Keep out of reach of children under 6 years of age. If more than used for brushing is accidently swallowed, get medical help or contact a Poison Control Center right away.
- Sensitivt teeth may indicate a serious problem that may need prompt care by a dentist. See your dentist if the problem persists or worsens. Do not use this product longer than 4 weeks unless recommended by a dentist or doctor.

Directions

- adults and children 12 years of age or older: apply at least a 1-inch strup of the tooth polish onto a soft bristle toothbrush. Brush teeth thoroughly for at least 1 minute twice a day (morning and evening) or as recommended by a dentist or doctor. Be sure to brush all sensitive areas of the teeth.
- children under 12 years of age: consult a dentist or doctor

INACTIVE INGREDIENT

Inactive Ingredients water, hydrated silica, glycerin, sorbitol, flavor, xanthan gum, stevia leaf extract, propanediol, poloxamer 407, zinc citrate, tetrasocium pyrophosphate, titanium dioxide, lauramidopropyl betaine, benzyl alcohol, sodium hydroxide, melaleuca alternifolia (tea tree) leaf oil.

Active Ingredient Purpose

Sodium fluoride (0.243%w/w)........................Anticavity

Potassium nitrate (5.0%w/w)...................Antisensitivity

Keep out of reach of children under 6 years of age. If more than used for brushing is accidently swallowed, get medical help or contact a Poison Control Center right away.

Do not use this product longer than 4 weeks unless recommended by a dentist or doctor.